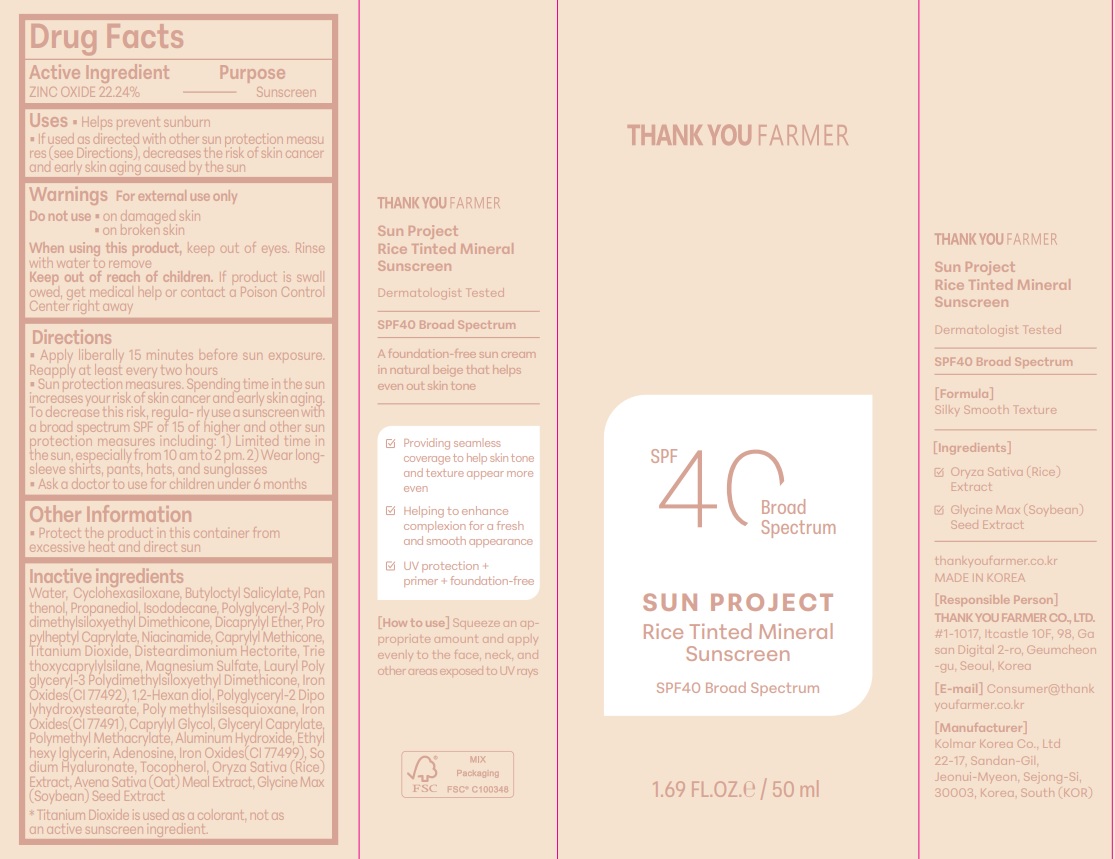 DRUG LABEL: THANKYOU FARMER Sun Project Rice Tinted Mineral Sunscreen
NDC: 70618-060 | Form: CREAM
Manufacturer: THANK YOU FARMER CO., LTD
Category: otc | Type: HUMAN OTC DRUG LABEL
Date: 20250311

ACTIVE INGREDIENTS: ZINC OXIDE 11.12 g/50 mL
INACTIVE INGREDIENTS: PROPYLHEPTYL CAPRYLATE; GLYCERYL CAPRYLATE; SOYBEAN; TOCOPHEROL; FERRIC OXIDE RED; OATMEAL; 1,2-HEXANEDIOL; DICAPRYLYL ETHER; FERRIC OXIDE YELLOW; ETHYLHEXYLGLYCERIN; CAPRYLYL GLYCOL; POLY(METHYL METHACRYLATE; 450000 MW); POLYGLYCERYL-2 DIPOLYHYDROXYSTEARATE; POLYGLYCERYL-3 POLYDIMETHYLSILOXYETHYL DIMETHICONE (4000 MPA.S); TRIETHOXYCAPRYLYLSILANE; ISODODECANE; DISTEARDIMONIUM HECTORITE; CYCLOMETHICONE 6; MAGNESIUM SULFATE ANHYDROUS; BUTYLOCTYL SALICYLATE; ALUMINUM HYDROXIDE; PANTHENOL; TITANIUM DIOXIDE; NIACINAMIDE; POLYMETHYLSILSESQUIOXANE (11 MICRONS); LAURYL POLYGLYCERYL-3 POLYDIMETHYLSILOXYETHYL DIMETHICONE (4000 MPA.S); CAPRYLYL TRISILOXANE; RICE GERM; HYALURONATE SODIUM; ADENOSINE; PROPANEDIOL; WATER

OTC Active Ingredient

Active Ingredient-ZINC OXIDE 22.24%

OTC-Purpose

Purpose-Sunscreen, Uses-Helps prevent sunburn

USES

Apply Liberally 15 minutes before sun exposure. Reapply at least every two hours, Sun Protection measures. Spending time in the sun increases your risk of skin cancer and early skin aging. T Decrease this risk, regularly use a sunscreen with a broad spectrum SPF of 15 of higher and other sun protection measures including: 1)Limited time in the sun, especially from 10am to 2pm. 2. sleeve shirts, pants, hats, and sunglasses. If product is swallowed medical help or contact a Poison Control Center right away

Keep Out Of Reach of Children- If product is swallowed, get medical help or contact a Poison Control Center right away

Do not use on damaged skin, on broken skin

Warning

For external use only. Do not use on damaged skin & broken skin.

Inactive Ingredients

Inactive Ingredients-WATER, CYCLOHEXASILOXANE, BUTYLOCTYL SALICYLATE, PANTHENOL, PROPANEDIOL, ISODODECANE, POLYGLYCERYL-3 POLYDIMETHYLSILOXYETHYL DIMETHICONE, DICAPRYLYL ETHER, PROPYLHEPTYL CAPRYLATE, NIACINAMIDE, CAPRYLYL METHICONE ,TITANIUM DIOXIDE, DISTEARDIMONIUM HECTORITE, TRIETHOXYCAPRYLYLSILANE, MAGNESIUM SULFATE, LAURYL POLYGLYCERYL-3 POLYDIMETHYLSILOXYETHYL DIMETHICONE, IRON OXIDES(CI 77492), 1,2- HEXANEDIOL, POLYGLYCERYL-2 DIPOLYHYDROXYSTEARATE ,POLYMETHYLSILSESQUIOXANE, IRON OXIDES(CI 77491), CAPRYLYL GLYCOL, GLYCERYL CAPRYLA POLYMETHYL METHACRYLATE, ALUMINUM HYDROXIDE, ETHYLHEXYLGLYCERIN, ADENOSINE, IRON OXIDES(CI 77499), SODIUM HYALURONATE, TOCOPHEROL O SATIVA (RICE) EXTRACT, AVENA SATIVA (OAT) MEAL EXTRACT, GLYCINE MAX (SOYBEAN) SEED EXTRACT

Other Safety Information-Protect the product in this container from excessive heat and direct sun

Incations & usage

Helps prevent sunburn. If used as directed with other sun protection measures (see Directions), decreases the risk of skin cancer and early skin aging caused by the sun.

Dosage & administration

Dosage & administration -Apply liberally 15 minutes before sun exposure. Reapply at least every two hours

Package Label Principal Display Panel-Thank Farmer, SPF40 Broad Spectrum, Sun Project Rice Tinted Mineral Sinscren, SPF40 Broad Spectrum, 1.69 FL.OZ/50ml